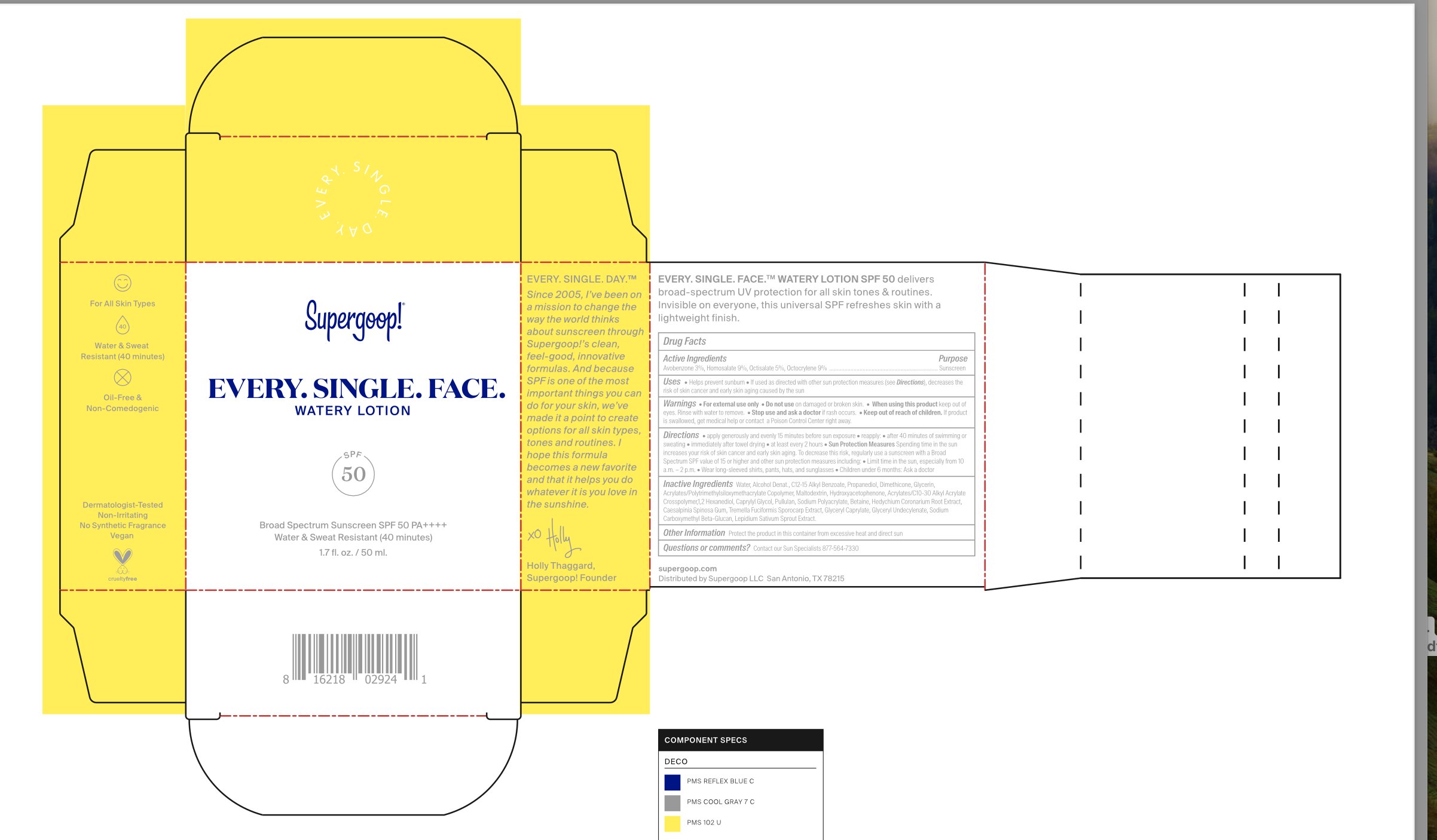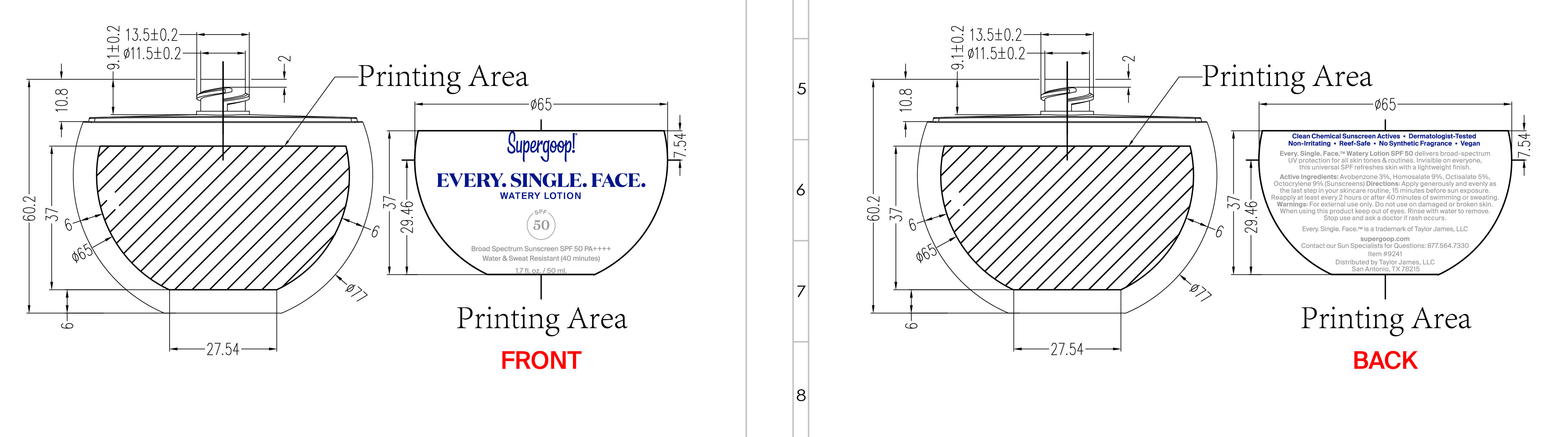 DRUG LABEL: Every. Single. Face. Watery SPF 50
NDC: 75936-652 | Form: LOTION
Manufacturer: Supergoop, LLC
Category: otc | Type: HUMAN OTC DRUG LABEL
Date: 20260109

ACTIVE INGREDIENTS: HOMOSALATE 9 g/100 mL; AVOBENZONE 3 g/100 mL; OCTISALATE 5 g/100 mL; OCTOCRYLENE 9 g/100 mL
INACTIVE INGREDIENTS: GARDEN CRESS SPROUT; LINALOOL, (+/-)-; TREMELLA FUCIFORMIS FRUITING BODY; PROPANEDIOL; DIMETHICONE; 1,2-HEXANEDIOL; PULLULAN; MALTODEXTRIN; ALKYL (C12-15) BENZOATE; GLYCERIN; HYDROXYACETOPHENONE; GLYCERYL MONOCAPRYLATE; CAPRYLYL GLYCOL; CAESALPINIA SPINOSA RESIN; SODIUM CARBOXYMETHYL .BETA.-GLUCAN (DS 0.65-0.85); HEDYCHIUM CORONARIUM ROOT; SODIUM POLYACRYLATE (8000 MW); WATER; ALCOHOL; BETAINE; GLYCERYL 1-UNDECYLENATE; ACRYLATE/ISOBUTYL METHACRYLATE/N-TERT-OCTYLACRYLAMIDE COPOLYMER (75000 MW); ACRYLATES/C10-30 ALKYL ACRYLATE CROSSPOLYMER (60000 MPA.S)

Every. Single. Face. Watery Lotion SPF 50

Active Ingredients Purpose

Avobenzone 3% Sunscreen

Homosalate 9%

Octisalate 5%

Octocrylene 9%

Uses

- Helps prevent sunburn
- If used as directed with other sun protection measures (see Directions), decreases the risk of skin cancer and early skin aging caused by the sun

Keep out of reach of children. If product is swallowed, get medical help or contact a Poison Control Center right away.

Stop use and ask a doctor if rash occurs.

Warnings

For external use only

Do not use on damaged or broken skin
When using this product keep out of eyes. Rinse with water to remove

Directions

- apply generously and evenly 15 minutes before sun exposure

reapply:

- after 40 minutes of swimming or sweating
- immediately after towel drying
- at least every 2 hours

Sun Protection Measures: Spending time in the sun increases your risk of early skin cancer and early skin aging. To decrease this risk, regularly use a sunscreen with a Broad Spectrum SPF calue of 15 or higher and other sun protection measures including:

- Limit time in the sun, especially from 10 a.m.-2p.m.
- Wear long-sleeved shirts, pants, hats, and sunglasses
- Reapply at least every 2 hours
- Children under 6 months: Ask a doctor

INACTIVE INGREDIENT

Inactive Ingredients: Water, Alcohol Denat., C12-15 Alkyl Benzoate, Propanediol, Dimethicone, Glycerin,
Acrylates/Polytrimethylsiloxymethacrylate Copolymer, Maltodextrin, Hydroxyacetophenone, Acrylates/C10-30 Alkyl Acrylate Crosspolymer, 1,2 Hexanediol, Caprylyl Glycol, Pullulan, Sodium Polyacrylate, Betaine, Hedychium Coronarium Root Extract, Caesalpinia Spinosa Gum, Tremella Fuciformis Sporocarp Extract, Glyceryl Caprylate, Glyceryl Undecylenate, Sodium Carboxymethyl Beta-Glucan, Lepidium Sativum Sprout Extract.

OTHER SAFETY INFORMATION

Protect the product in this container from excessive heat and direct sun.

PACKAGE LABEL

Supergoop!

EVERY. SINGLE. FACE.

WATERY LOTION

SPF 50

Broad Spectrum Sunscreen SPF 50 PA++++

Water & Sweat Resistant (40 minutes)

1.7 fl. oz./ 50 ml.